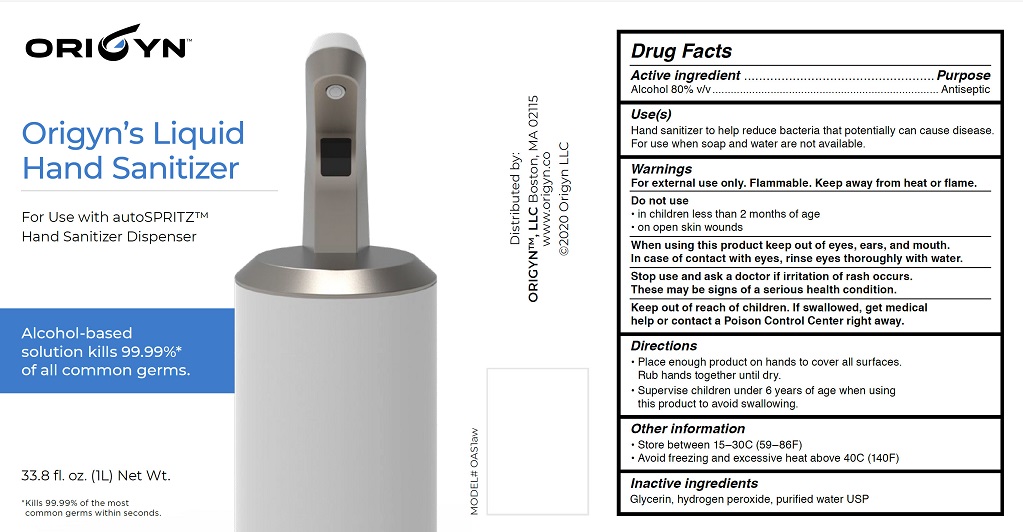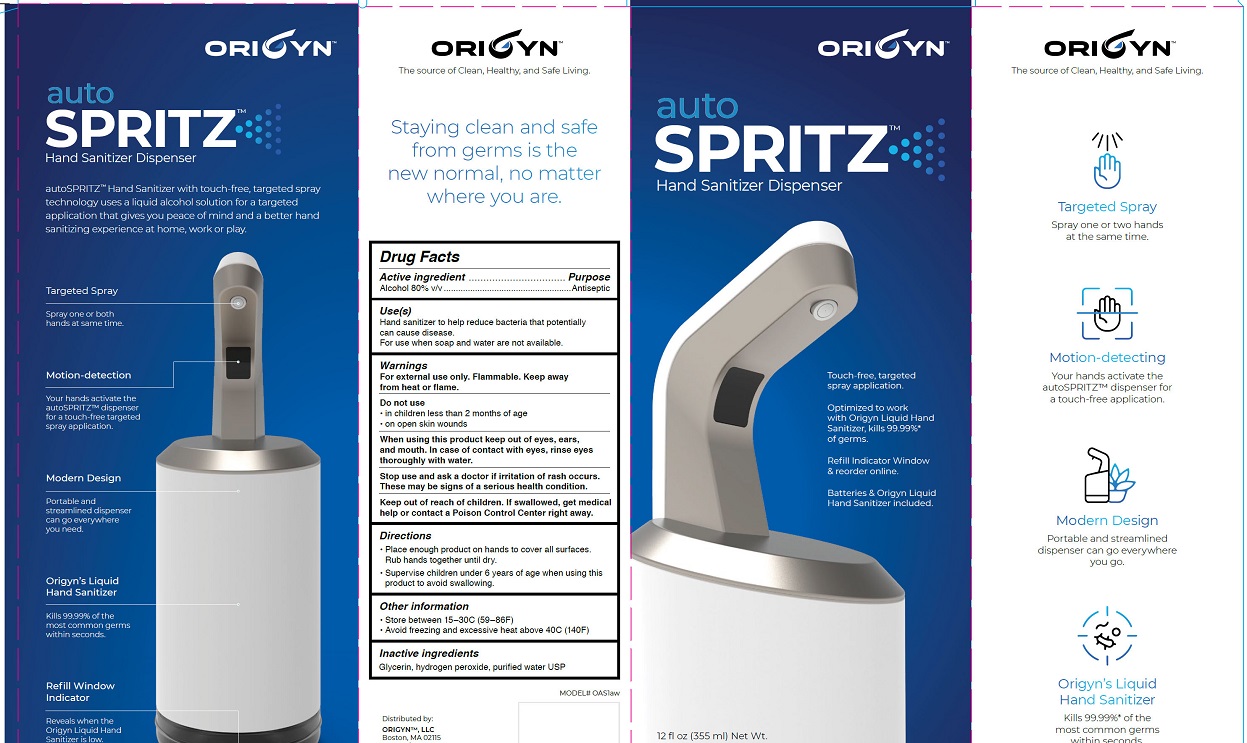 DRUG LABEL: AutoSpritz
NDC: 79281-010 | Form: SOLUTION
Manufacturer: ORIGYN LLC
Category: otc | Type: HUMAN OTC DRUG LABEL
Date: 20200701

ACTIVE INGREDIENTS: ALCOHOL 80 L/100 L
INACTIVE INGREDIENTS: GLYCERIN 1.45 L/100 L; HYDROGEN PEROXIDE 0.125 L/100 L; WATER 18.425 L/100 L

ACTIVE INGREDIENTS

Alcohol 80% v/v

INACTIVE INGREDIENTS

Glycerin, hydrogen peroxide, purified water USP

PURPOSE

Antiseptic

Keep out of reach of children. If swallowed, get medical help, or contact a Poison Control Center right away.

INDICATIONS & USAGE

- Hand sanitizer to help reduce bacteria that potentially can cause disease.
- For use when soap and water are not available

WARNINGS

- For external use only. Flammable. Keep away from heat or flame.
- Do not use
  - for children less than 2 months of age
  - on open skin wounds
- When using this product keep out of eyes, ears, and mouth. In case of contact with eyes, rinse eyes thoroughly with water.
- Stop use and ask a doctor if irritation of rash occurs. These may be signs of a serious health condition.
- Keep out of reach of children. If swallowed, get medical help or contact a Poison Control Center right away.

DOSAGE & ADMINISTRATION

• Place enough product on hands to cover all surfaces. Rub hands together until dry.
• Supervise children under 6 years of age when using this product to avoid swallowing.